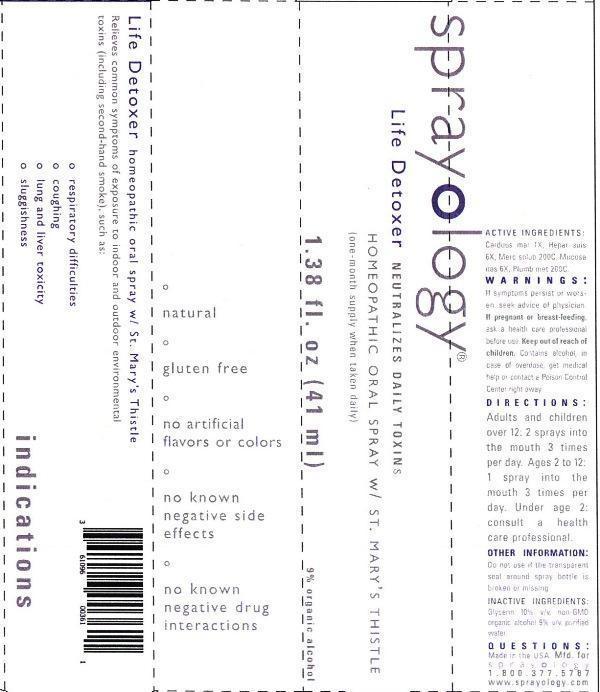 DRUG LABEL: Sprayology Life Detoxer
NDC: 61096-0023 | Form: LIQUID
Manufacturer: Eight and Company
Category: homeopathic | Type: HUMAN OTC DRUG LABEL
Date: 20140225

ACTIVE INGREDIENTS: MILK THISTLE 1 [hp_X]/41 mL; PORK LIVER 6 [hp_X]/41 mL; MERCURIUS SOLUBILIS 200 [hp_C]/41 mL; SUS SCROFA NASAL MUCOSA 6 [hp_X]/41 mL; LEAD 200 [hp_C]/41 mL
INACTIVE INGREDIENTS: GLYCERIN; ALCOHOL; WATER

Sprayology Life Detoxer

ACTIVE INGREDIENT

Active Ingredients: Carduus marianus 1X, Hepar suis 6X, Mercurius solubilis 200C, Mucosa nasalis suis 6X, Plumbum metallicum 200C

WARNINGS

Warnings: If symptoms persist or worsen, seek advice of physician. If pregnant or breast-feeding, ask a health care professional before use. Keep out of reach of children. Contains alcohol, in case of overdose, get medical help or contact a Poison Control Center right away.

Keep out of reach of children.

Directions:

- Adults and children over 12: 2 sprays into the mouth 3 times per day.
- Ages 2 to 12: 1 spray into the mouth 3 times per day.
- Under age 2: consult a health care professional.

PURPOSE

Relieves common symptoms of exposure to indoor and outdoor environmental toxins (including second-hand smoke), such as:

- respiratory difficulties
- coughing
- lung and liver toxicity
- sluggishness

Other Information: Do not use if the transparent seal around spray bottle is broken or missing.

INACTIVE INGREDIENT

Inactive Ingredients: Glycerin 10% v/v, non-GMO organic alcohol 9% v/v and purified water.

INDICATIONS AND USAGE

Relieves common symptoms of exposure to indoor and outdoor environmental toxins (including second-hand smoke), such as:

° respiratory difficulties

° coughing

° lung and liver toxicity

° sluggishness

° natural

° gluten free

° no artificial flavors or colors

° no known negative side effects

° no known negative drug interactions